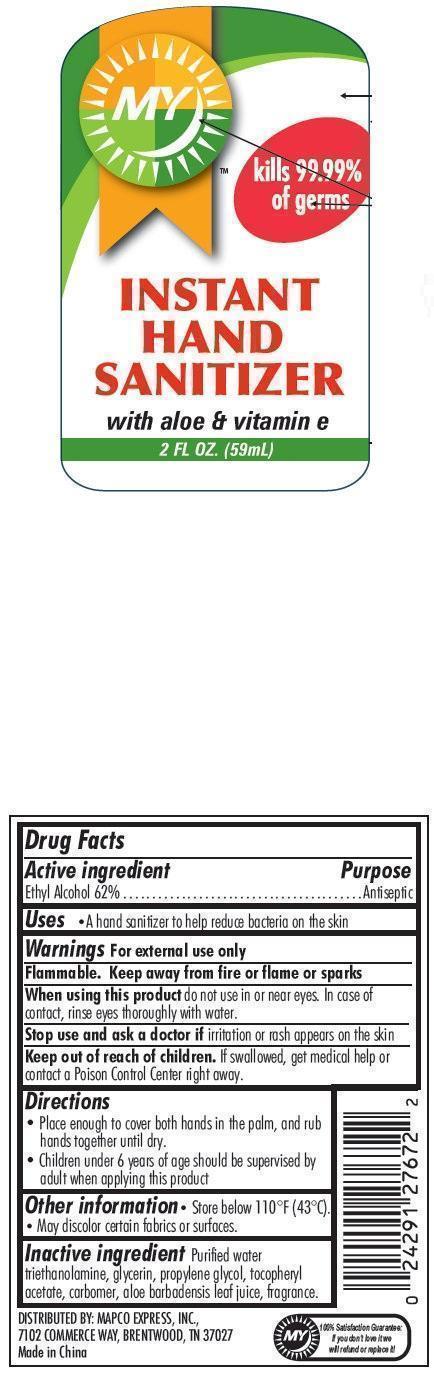 DRUG LABEL: MY INSTANT HAND SANITIZER with aloe and vitamin e
                
NDC: 59086-085 | Form: GEL
Manufacturer: Mapco Express
Category: otc | Type: HUMAN OTC DRUG LABEL
Date: 20130703

ACTIVE INGREDIENTS: ALCOHOL 620 mg/1 mL
INACTIVE INGREDIENTS: WATER; TROLAMINE; GLYCERIN; PROPYLENE GLYCOL; .ALPHA.-TOCOPHEROL ACETATE; ALOE VERA LEAF

MY INSTANT HAND SANITIZER with aloe & vitamin e

Active ingredient

Ethyl Alcohol 62%

Purpose

Antiseptic

Uses

- A hand sanitizer to help reduce bacteria on the skin

Warnings

For external use only

Flammable.

Keep away from fire or flame or sparks

When using this product

do not use in or near eyes. In case of contact, rinse eyes thoroughly with water.

Stop use and ask a doctor if

irritation or rash appears on the skin

Keep out of reach of children.

If swallowed, get medical help or contact a Poison Control Center right away.

Directions

- Place enough to cover both hands in the palm, and rub hands together until dry.
- Children under 6 years of age should be supervised by adult when applying this product

Other information

Store below 110°F (43°C).• May discolor certain fabrics or surfaces.

Inactive ingredient

Purified water triethanolamine, glycerin, propylene glycol, tocopheryl acetate, carbomer, aloe barbadensis leaf juice, fragrance.

DISTRIBUTED BY:

MAPCO EXPRESS, INC.,
7102 COMMERCE WAY, BRENTWOOD, TN 37027
Made in China

MY 100% Satisfaction Guarantee:
If you don’t love it we will refund or replace it!

0 24291 27672 2

PACKAGE LABEL

MY kills 99.99% of germs

INSTANT HAND SANITIZER with aloe and vitamin e

2 FL OZ. (59mL)